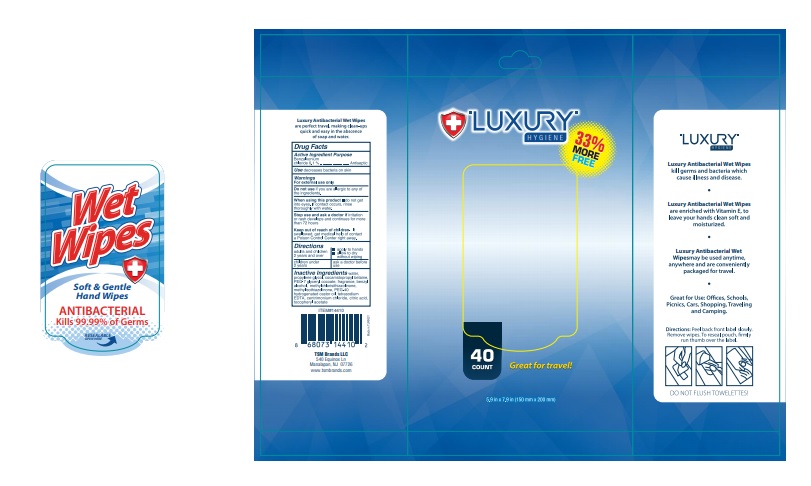 DRUG LABEL: Antibacterial Wet Wipes
NDC: 76772-008 | Form: SWAB
Manufacturer: TSM ITHALAT IHRACAT SANAYI VE DIS TICARET LIMITED SIRKETI
Category: otc | Type: HUMAN OTC DRUG LABEL
Date: 20200507

ACTIVE INGREDIENTS: BENZALKONIUM CHLORIDE 0.1 g/1 1
INACTIVE INGREDIENTS: PROPYLENE GLYCOL; COCAMIDOPROPYL BETAINE; PEG-7 GLYCERYL COCOATE; 2-METHYL-1,2-BENZOISOTHIAZOLIN-3-ONE; PEG-40 HYDROGENATED LANOLIN; EDETATE SODIUM; CITRIC ACID ACETATE; .ALPHA.-TOCOPHEROL ACETATE, D-; METHYLISOTHIAZOLINONE; WATER; CETRIMONIUM CHLORIDE

ANTIBACTERIAL WET WIPES 40

Active ingredient

Benzalkonium chloride 0.1%...........Antiseptic

Purpose

Antibacterial

Use

decreases bacteria on skin

Warnings

For external use only.

Keep out of reach of children

if swallowed

get medical help or contact a Poison Control Center right away.

Do not use

if you are allergic to any of the ingredients.

When using this product

do not get into eyes.

If contact occurs, rinse thoroughly with water.

Stop use and ask a doctor

if irritation or rash

develops and continues for more than 72 hours

Keep out of reach of children.

If swallowed, get medical help or contact
a Poison Control Center right away.

Directions

For adults and children of 2 years and over use

on hands and face to clean and refresh, allow

skin to air dry.

For children under 2 years ask a doctor before use.

INACTIVE INGREDIENT

water, propylene glycol,

cocamidopropyl betaine, poly(hexamethyleneguanidine),PEG-7 glyceryl cocoate ,

hydrochloride, glycine, tetrasodium EDTA, tocopheryl acetate, citric acid,

fragrance, methylchloroisothiazolinone, methylisothiazolinone,

PEG-40 hydrogenated castor oil.